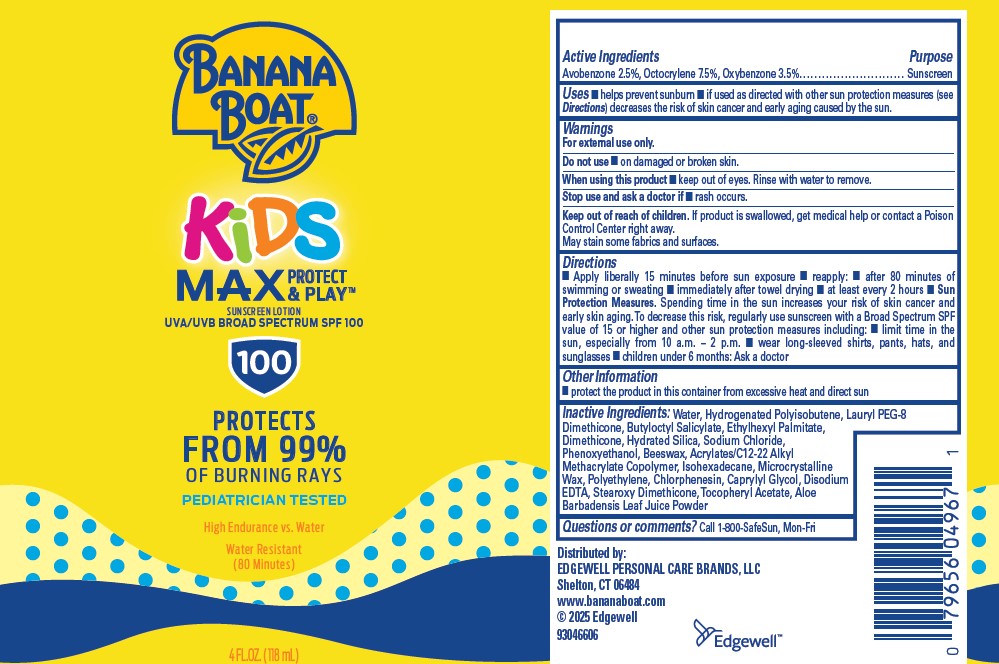 DRUG LABEL: BANANA BOAT
NDC: 63354-391 | Form: LOTION
Manufacturer: Edgewell Personal Care Brands LLC
Category: otc | Type: HUMAN OTC DRUG LABEL
Date: 20250813

ACTIVE INGREDIENTS: AVOBENZONE 2.5 g/100 g; OCTOCRYLENE 7.5 g/100 g; OXYBENZONE 3.5 g/100 g
INACTIVE INGREDIENTS: HYDROGENATED POLYISOBUTENE (450 MW); HYDRATED SILICA; WATER; BUTYLOCTYL SALICYLATE; ALPHA-TOCOPHEROL ACETATE; MICROCRYSTALLINE WAX; POLYETHYLENE; BEESWAX; ISOHEXADECANE; DIMETHICONE; CAPRYLYL GLYCOL; PHENOXYETHANOL; ALOE BARBADENSIS LEAF POWDER; ETHYLHEXYL PALMITATE; EDETATE DISODIUM; CHLORPHENESIN; LAURYL PEG-8 DIMETHICONE (300 CPS); SODIUM CHLORIDE

Active Ingredients

Avobenzone 2.5%, Octocrylene 7.5%, Oxybenzone 3.5%

Purpose

Sunscreen

Uses

■ helps prevent sunburn ■ if used as directed with other sun protection measures (see Directions) decreases the risk of skin cancer and early aging caused by the sun.

Warnings

For external use only.

May stain some fabrics and surfaces.

Do not use

■ on damaged or broken skin.

When using this product

■ keep out of eyes. Rinse with water to remove.

Stop use and ask a doctor if

■ rash occurs.

Keep out of reach of children.

If product is swallowed, get medical help or contact a Poison Control Center right away.

Directions

■ Apply liberally 15 minutes before sun exposure ■ reapply: ■ after 80 minutes of swimming or sweating ■ immediately after towel drying ■ at least every 2 hours ■ Sun Protection Measures. Spending time in the sun increases your risk of skin cancer and early skin aging. To decrease this risk, regularly use sunscreen with a Broad Spectrum SPF value of 15 or higher and other sun protection measures including: ■ limit time in the sun, especially from 10 a.m. – 2 p.m. ■ wear long-sleeved shirts, pants, hats, and sunglasses ■ children under 6 months: Ask a doctor

Other Information

■protect the product in this container from excessive heat and direct sun

Inactive Ingredients:

Water, Hydrogenated Polyisobutene, Lauryl PEG-8 Dimethicone, Butyloctyl Salicylate, Ethylhexyl Palmitate, Dimethicone, Hydrated Silica, Sodium Chloride, Phenoxyethanol, Beeswax, Acrylates/C12-22 Alkyl Methacrylate Copolymer, Isohexadecane, Microcrystalline Wax, Polyethylene, Chlorphenesin, Caprylyl Glycol, Disodium EDTA, Stearoxy Dimethicone, Tocopheryl Acetate, Aloe Barbadensis Leaf Juice Powder

Questions or comments?

Call 1-800-SafeSun, Mon-Fri

PRINICIPAL DISPLAY PANEL

BANANA
BOAT
KIDS
MAX PROTECT & PLAY
SUNSCREEN LOTION
UVA/UVB BROAD SPECTRUM SPF 100
100
PROTECTS
FROM 99%
OF BURNING RAYS
PEDIATRICIAN TESTED
HIGH ENDURANCE VS. WATER
WATER RESISTANT
(80 MINUTES)
4 FL. OZ. (118 mL)